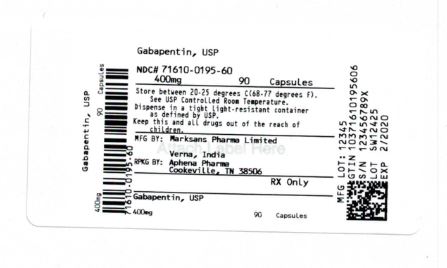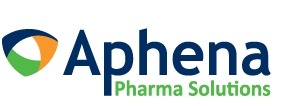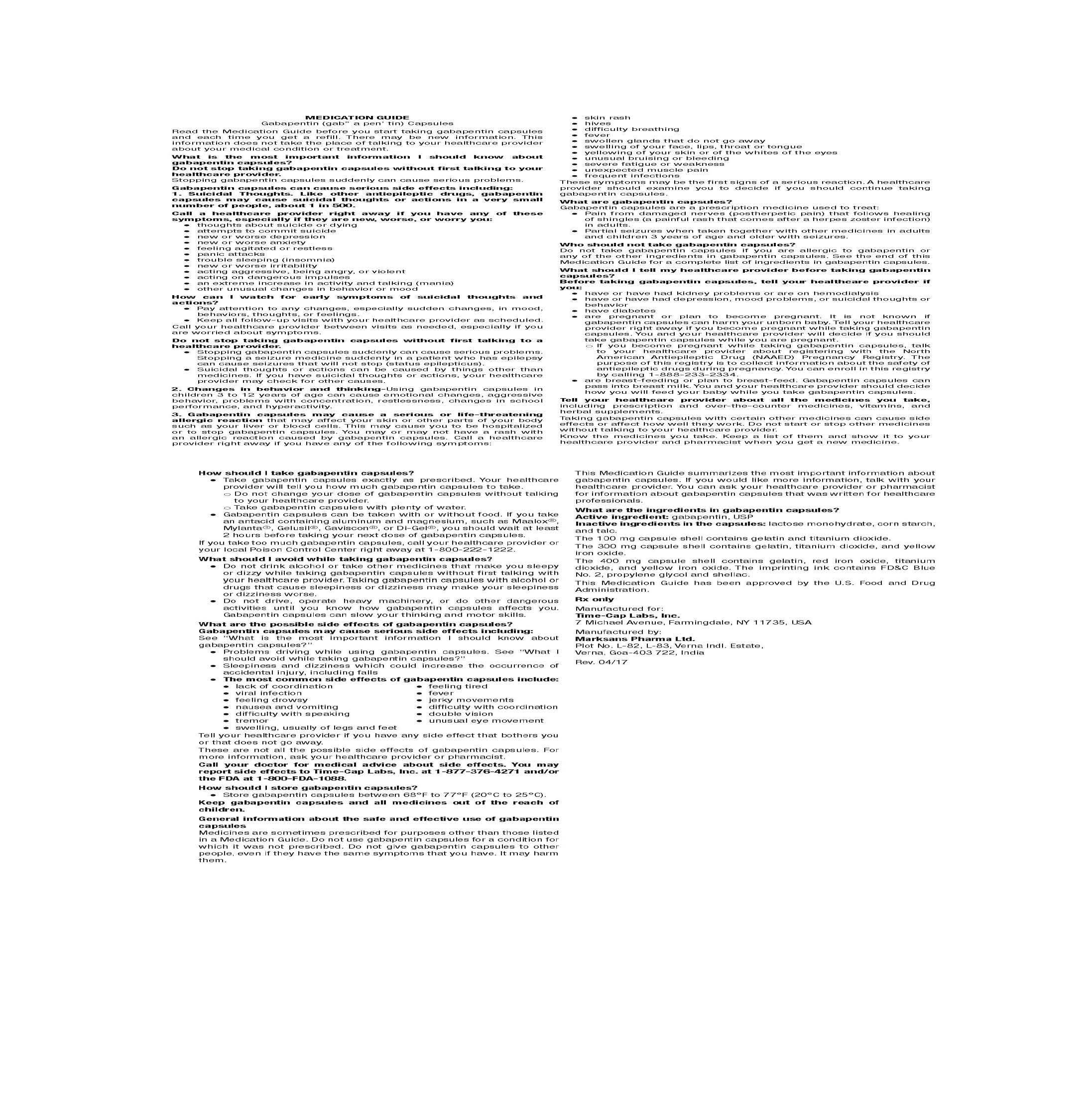 DRUG LABEL: GABAPENTIN
NDC: 71610-195 | Form: CAPSULE
Manufacturer: Aphena Pharma Solutions - Tennessee, LLC
Category: prescription | Type: HUMAN PRESCRIPTION DRUG LABEL
Date: 20190801

ACTIVE INGREDIENTS: GABAPENTIN 400 mg/1 1
INACTIVE INGREDIENTS: LACTOSE MONOHYDRATE; STARCH, CORN; TALC; GELATIN; TITANIUM DIOXIDE; FERRIC OXIDE YELLOW; FD&C BLUE NO. 2; PROPYLENE GLYCOL; SHELLAC

HOW SUPPLIED

100 mg Capsules (White/White colored, size '3' hard gelatin capsules with "103" printed on body of capsules containing white to off white granular powder) Bottles of 100 & 500

HOW SUPPLIED

300 mg Capsules (Yellow/Yellow colored, size '1' hard gelatin capsules with "104" printed on body of capsules containing white to off white granular powder) Bottles of 100 & 500

HOW SUPPLIED

400 mg Capsules (Orange/Orange colored, size '0' hard gelatin capsules with "105" printed on body of capsules containing white to off white granular powder) Bottles of 100 & 500

Repackaging Information

Please reference the How Supplied section listed above for a description of individual tablets. This drug product has been received by Aphena Pharma - TN in a manufacturer or distributor packaged configuration and repackaged in full compliance with all applicable cGMP regulations. The package configurations available from Aphena are listed below:

Count | 400 mg
90 | 71610-195-60
270 | 71610-195-92

Store between 20°-25°C (68°-77°F). See USP Controlled Room Temperature. Dispense in a tight light-resistant container as defined by USP. Keep this and all drugs out of the reach of children.

Repackaged by:
Cookeville, TN 38506
20190801JH

PRINCIPAL DISPLAY PANEL - 400 mg

NDC 71610-195 - Gabapentin, USP 400 mg - Rx Only